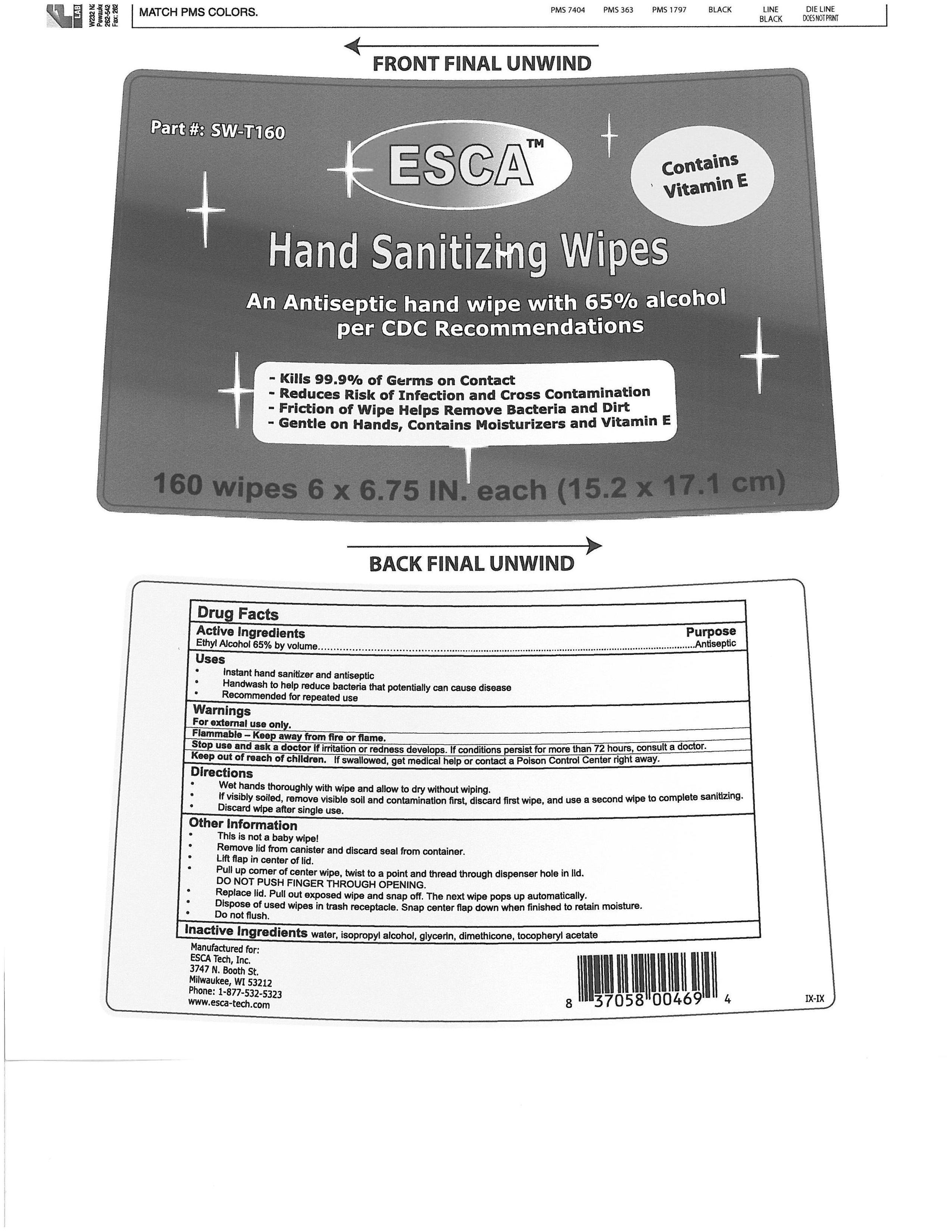 DRUG LABEL: ESCA Hand Sanitizing Wipes
NDC: 52033-001 | Form: LIQUID
Manufacturer: ESCA Tech, Inc.
Category: otc | Type: HUMAN OTC DRUG LABEL
Date: 20100301

ACTIVE INGREDIENTS: Alcohol 65 mL/100 mL
INACTIVE INGREDIENTS: Water; Isopropyl Alcohol; Glycerin; Dimethicone

Drug Facts

Active Ingredient Purpose
Ethyl Alcohol 65% by volume...................Antiseptic

Uses

Instant hand sanitizer and antiseptic

Handwash to help reduce bacteria that potentially can cause disease

Recommended for repeated use

Warnings

For external use only.

Flammable - Keep away from fire or flame.

Stop use and ask a doctor if irritation or redness develops.

If condition persists for more than 72 hours, consult a doctor.

Keep out of reach of children.

If swallowed, get medical help or contact a Poison Control Center right away.

Directions
Wet hands thoroughly with wipe and allow to dry without wiping.
If visibly soiled, remove visible soil and contamination first, discard first wipe, and use a second wipe to complete sanitizings.
Discard wipe after single use.

Other Information
This is not a baby wipe!
Remove lid from canister and discard seal from container.
Lift flap in center of lid.
Pull up corner of center wipe, twist to a point and thread through dispenser hole in lid.
DO NOT PUSH FINGER THROUGH OPENING.
Replace lid. Pull out exposed wipe and snap off. The next wipe pops out automatically.
Dispose of used wipes in trash receptacle. Snap center flap down when finished to retain moisture.
Do not flush.

Inactive Ingredients
water, isopropyl alcohol, glycerin, dimethicone, tocopheryl acetate

PACKAGE LABEL

Part # SW-T160

Contains Vitamin E

ESCA Hand Sanitizing Wipes

An Antiseptic hand wipe with 65% alcohol per CDC Recommendations

Kills 99.9% of Germs on Contact

Reduces Risk of Infection and Cross Contamination

Friction of Wipe Helps Remove Bacteria and Dirt

Gentle on Hands, Contains Moisturizers and Vitamin E

160 wipes 6 x 6.75 IN. each (15.2 x 17.1 cm)